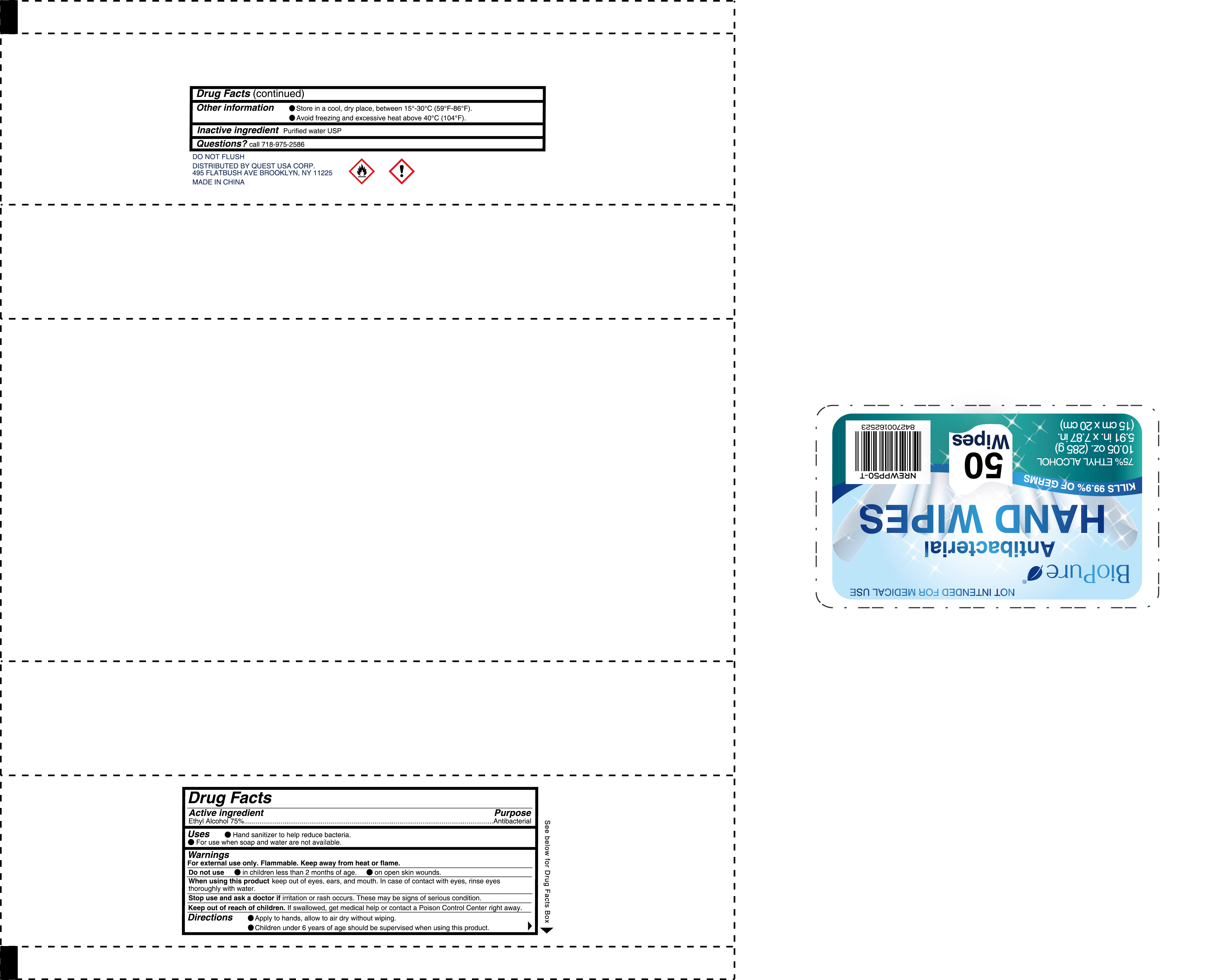 DRUG LABEL: Biopure  Antibacterial Hand Wipes
NDC: 79866-009 | Form: CLOTH
Manufacturer: Osike Cosmetics Co., Ltd.
Category: otc | Type: HUMAN OTC DRUG LABEL
Date: 20220120

ACTIVE INGREDIENTS: ALCOHOL 75 g/100 1
INACTIVE INGREDIENTS: WATER

79866-009
Antibacterial Hand Wipes

Active Ingredient(s)

Ethyl Alcohol 75%

Purpose

Antiseptic

Use

●Hand sanitizer to help reduce bacteria
●For use when soap and water are not available.

Warnings

For external use only. Flammable.Keep away from heat or flame.

Do not use
●in children less than 2 mouths of age.
●on open skin wounds

When using this product
Keep out of eyes,ears, and mouth. In case of contact with eyes, rinse eyes thoroughly with water.

Stop use and ask a doctor if irritation or rash occurs. These may be signs of serious condition.

Keep out of reach of children. If swallowed. get medical help or contact a Poison Control Center right away.

Do not use

●in children less than 2 mouths of age.
●on open skin wounds

When using this product
Keep out of eyes,ears, and mouth. In case of contact with eyes, rinse eyes thoroughly with water.

Stop use and ask a doctor if irritation or rash occurs. These may be signs of serious condition.

Keep out of reach of children. If swallowed. get medical help or contact a Poison Control Center right away.

Stop use and ask a doctor if irritation or rash occurs. These may be signs of serious condition.

Keep out of reach of children. If swallowed. get medical help or contact a Poison Control Center right away.

Directions

●Apply to hands, allow to air dry without wiping.
●Children under 6 years of age should be supervised when using this product

Other information

●Store in a cool, dry place,between 15°-30°C(59°F-86°F)。
●Avoid freezing and excessive heat above 40°C(104°F).

Inactive ingredients

Purified water USP